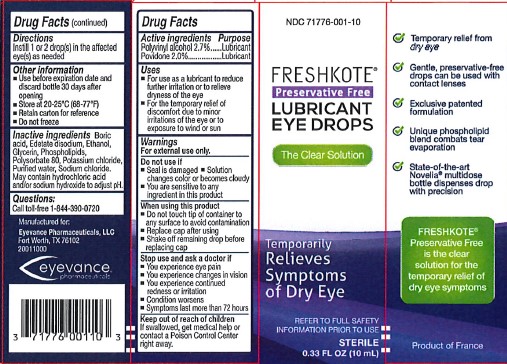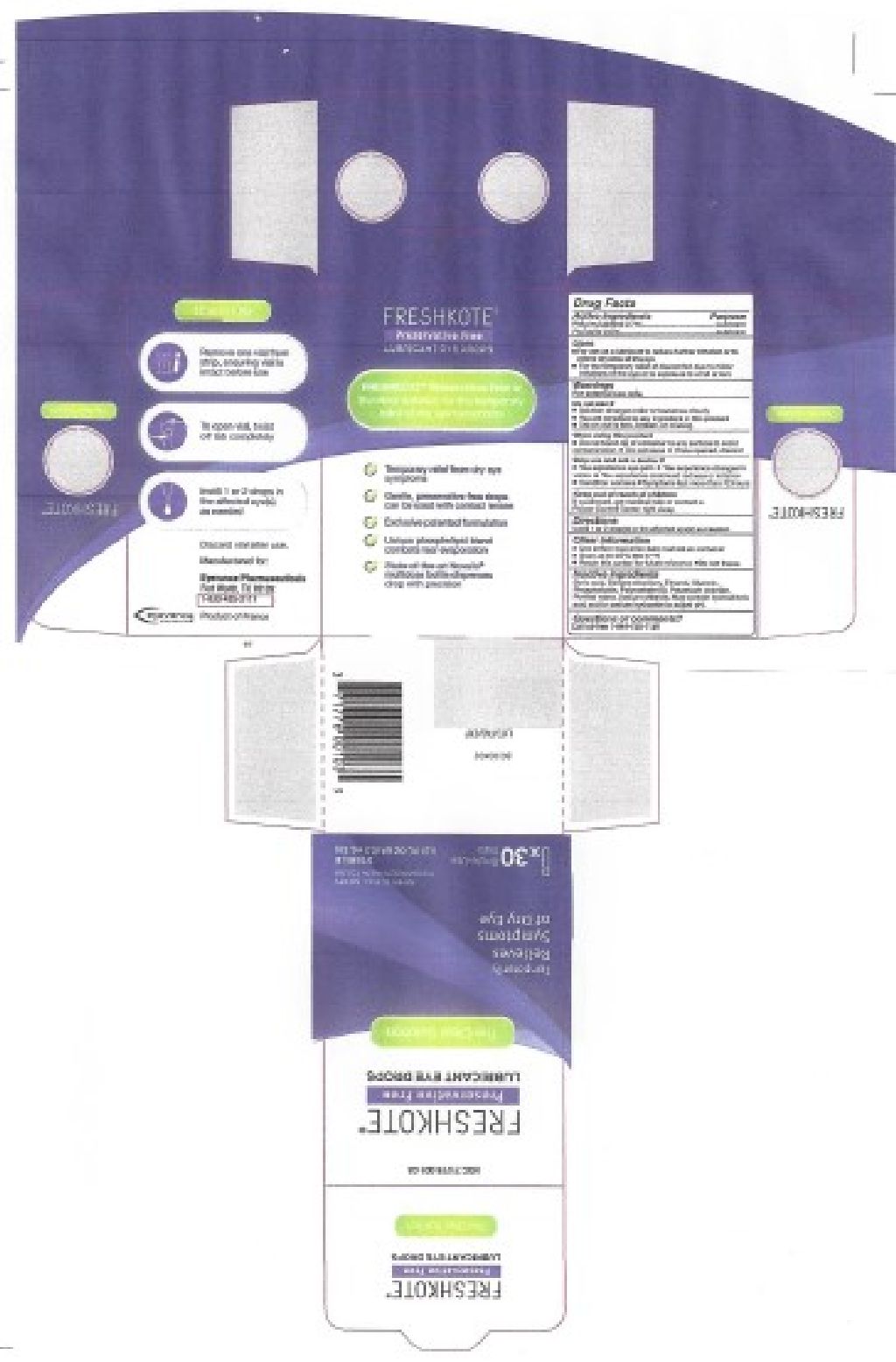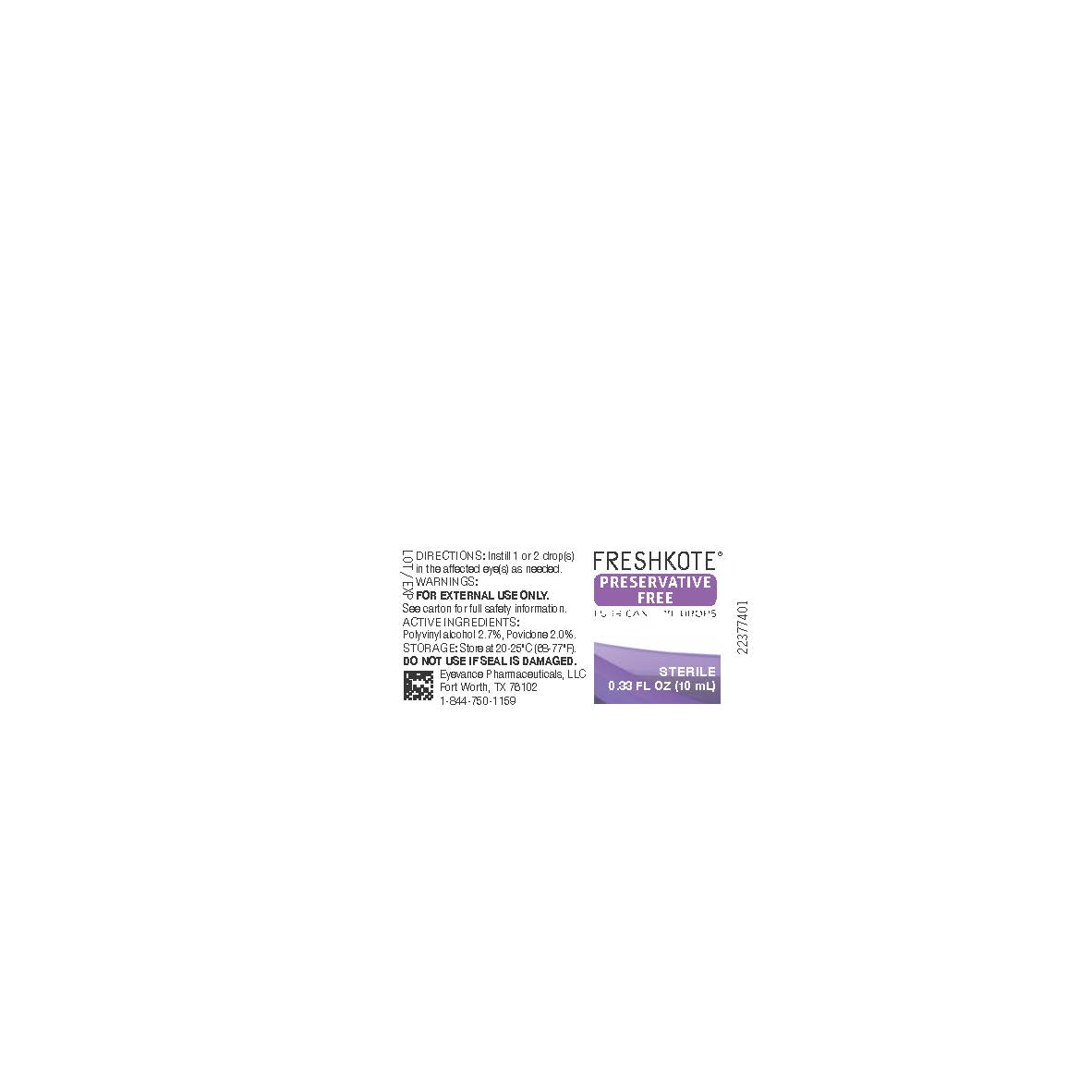 DRUG LABEL: FreshKote Preservative Free Lubricant Eye Drops
NDC: 71776-001 | Form: SOLUTION
Manufacturer: Eyevance Pharmaceuticals
Category: otc | Type: HUMAN OTC DRUG LABEL
Date: 20231005

ACTIVE INGREDIENTS: POVIDONE 20 g/1000 mL; POLYVINYL ALCOHOL, UNSPECIFIED 27 g/1000 mL
INACTIVE INGREDIENTS: BORIC ACID; EDETATE DISODIUM; ALCOHOL; GLYCERIN; EGG PHOSPHOLIPIDS; POLYSORBATE 80; POTASSIUM CHLORIDE; SODIUM CHLORIDE; WATER

FRESHKOTE®
Preservative Free
LUBRICANT EYE DROPS

Active Ingredients Purpose

Polyvinyl Alcohol 2.7%.........Lubricant

Povidone 2.0%....................Lubricant

Uses

- For use as a lubricant to reduce further irritation or to relieve dryness of the eye

Warnings

For external use only.

Do not use if

- Seal is damaged
- Solution changes color or becomes cloudy
- You are sensitive to any ingredient in this product

Stop use and ask a doctor if

- You experience eye pain
- You experience changes in vision
- You experience continued redness or irritation
- Condition worsens
- Symptoms last more than 72 hours

Keep out of reach of children

If swallowed, get medical help or contact a Poison Control Center right away.

Directions

Instill 1 or 2 drop(s) in the affected eye(s) as needed

Other information

- Use before expiration date and discard bottle 30 days after opening
- Store at 20-25οC(68-77οF)
- Retain carton for reference
- Do not freeze

Inactive ingredients

Boric acid, Edetate disodium, Ethanol, Glycerin, Phospholipids, Polysorbate 80, Potassium chloride, Purified water, Sodium chloride. May contain hydrochloric acid and/or sodium hydroxide to adjust pH.

Purpose

For the temporary relief of discomfort due to minor irritations of the eye or to exposure to wind or sun

When using this product

- Do not touch tip of container to any surface to avoid contamination
- Replace cap after using
- Shake off remaining drop before replacing cap